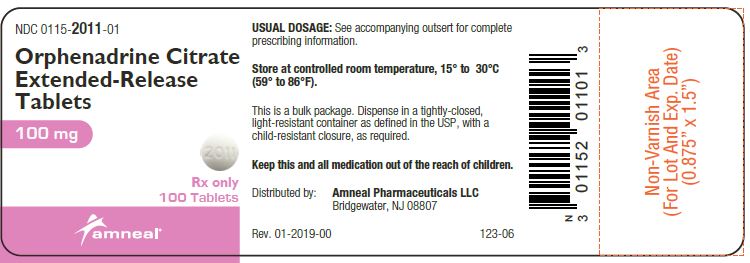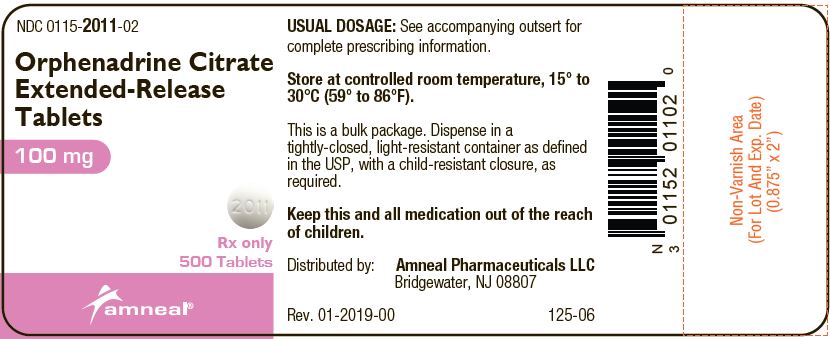 DRUG LABEL: Orphenadrine Citrate
NDC: 0115-2011 | Form: TABLET, EXTENDED RELEASE
Manufacturer: Amneal Pharmaceuticals of New York LLC
Category: prescription | Type: HUMAN PRESCRIPTION DRUG LABEL
Date: 20191227

ACTIVE INGREDIENTS: ORPHENADRINE CITRATE 100 mg/1 1
INACTIVE INGREDIENTS: ETHYLCELLULOSES; POVIDONE; LACTOSE MONOHYDRATE; MAGNESIUM STEARATE

Orphenadrine Citrate Extended-Release Tablets
(100 mg)

Rx only

DESCRIPTION

Orphenadrine citrate is the citrate salt of orphenadrine (2-dimethylaminoethyl-2-methylbenzhydryl ether citrate). It occurs as a white, crystalline powder having a bitter taste. It is practically odorless; sparingly soluble in water, slightly soluble in alcohol.

Each orphenadrine citrate extended-release tablet contains 100 mg orphenadrine citrate, USP. Orphenadrine citrate extended-release tablets also contain ethylcellulose NF, povidone USP, lactose monohydrate NF, and magnesium stearate NF.

CLINICAL PHARMACOLOGY

The mode of therapeutic action has not been clearly identified, but may be related to its analgesic properties. Orphenadrine citrate does not directly relax tense skeletal muscles in man.

Orphenadrine citrate also possesses anti-cholinergic actions.

INDICATIONS AND USAGE

Orphenadrine citrate extended-release tablets are indicated as an adjunct to rest, physical therapy, and other measures for the relief of discomfort associated with acute painful musculo skeletal conditions.

CONTRAINDICATIONS

Contraindicated in patients with glaucoma, pyloric or duodenal obstruction, stenosing peptic ulcers, prostatic hypertrophy or obstruction of the bladder neck, cardio-spasm (megaesophagus) and myasthenia gravis.

Contraindicated in patients who have demonstrated a previous hypersensitivity to the drug.

WARNINGS

Some patients may experience transient episodes of light-headedness, dizziness or syncope. Orphenadrine citrate may impair the ability of the patient to engage in potentially hazardous activities such as operating machinery or driving a motor vehicle; ambulatory patients should therefore be cautioned accordingly.

PRECAUTIONS

Confusion, anxiety and tremors have been reported in few patients receiving propoxyphene and orphenadrine concomitantly. As these symptoms may be simply due to an additive effect, reduction of dosage and/or discontinuation of one or both agents is recommended in such cases.

Orphenadrine citrate should be used with caution in patients with tachycardia, cardiac decompensation, coronary insufficiency, cardiac arrhythmias.

Safety of continuous long-term therapy with orphenadrine has not been established. Therefore, if orphenadrine is prescribed for prolonged use, periodic monitoring of blood, urine and liver function values is recommended.

Pregnancy

Pregnancy Category C. Animal reproduction studies have not been conducted with orphenadrine citrate. It is also not know whether orphenadrine citrate can cause fetal harm when administered to a pregnant woman or can affect reproduction capacity. Orphenadrine citrate should be given to a pregnant woman only if clearly needed.

Pediatric Use

Safety and effectiveness in pediatric patients have not been established.

ADVERSE REACTIONS

Adverse reactions of orphenadrine are mainly due to the mild anti-cholinergic action of orphenadrine, and are usually associated with higher dosage. Dryness of the mouth is usually the first adverse effect to appear. When the daily dose is increased, possible adverse effects include: tachycardia, palpitation, urinary hesitancy or retention, blurred vision, dilation of pupils, increased ocular tension, weakness, nausea, vomiting, headache, dizziness, constipation, drowsiness, hypersensitivity reactions, pruritus, hallucinations, agitation, tremor, gastric irritation, and rarely urticaria and other dermatoses. Infrequently, an elderly patient may experience some degree of mental confusion. These adverse reactions can usually be eliminated by reduction in dosage. Very rare cases of aplastic anemia associated with the use of orphenadrine tablets have been reported. No causal relationship has been established.

To report SUSPECTED ADVERSE REACTIONS, contact Amneal Pharmaceuticals at 1-877-835-5472 or FDA at 1-800-FDA-1088 or www.fda.gov/medwatch.

DRUG ABUSE AND DEPENDENCE

Orphenadrine has been chronically abused for its euphoric effects.[1] The mood elevating effects may occur at therapeutic doses of orphenadrine.[2]

OVERDOSAGE

Orphenadrine is toxic when overdosed and typically induces anticholinergic effects.[3] In a review of orphenadrine toxicity, the minimum lethal dose was found to be 2 grams to 3 grams for adults; however, the range of toxicity is variable and unpredictable.[4] Treatment for orphenadrine overdose is evacuation of stomach contents (when necessary), charcoal at repeated doses, intensive monitoring, and appropriate supportive treatment of any emergent anticholinergic effects.[5]

DOSAGE AND ADMINISTRATION

Orphenadrine citrate extended-release tablets: Adults - Two tablets per day; one in the morning and one in the evening.

HOW SUPPLIED

Orphenadrine Citrate Extended-release Tablets, 100 mg - Each round, white, convex tablet imprinted with “G” on one side and “2011” on the other side.

They are available as follows:

Bottles of 100: NDC 0115-2011-01

Bottles of 500: NDC 0115-2011-02

Store at controlled room temperature 15° to 30°C (59° to 86°F).

Dispense in tightly-closed, light-resistant container (USP).

Distributed by:
Amneal Pharmaceuticals LLC
Bridgewater, NJ 08807

124-05

Rev. 01-2019-00

PRINCIPAL DISPLAY PANEL - 100 mg Tablet Bottle Label

NDC 0115-2011-01

Orphenadrine Citrate Extended-Release Tablets

100 mg

Rx only

100 TABLETS

PRINCIPAL DISPLAY PANEL - 100 mg Tablet Bottle Label

NDC 0115-2011-02

Orphenadrine Citrate Extended-Release Tablets

100 mg

Rx only

500 TABLETS